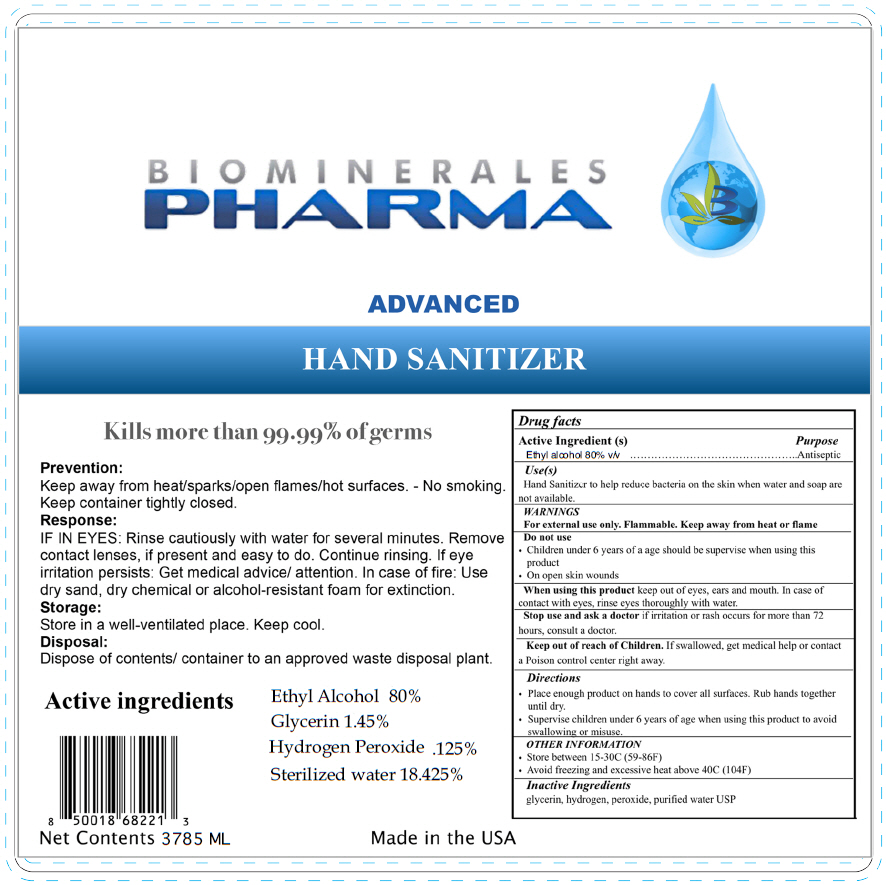 DRUG LABEL: ADVANCED HAND SANITIZER
NDC: 77110-100 | Form: GEL
Manufacturer: Biominerales Pharma, LLC
Category: otc | Type: HUMAN OTC DRUG LABEL
Date: 20200506

ACTIVE INGREDIENTS: ALCOHOL 0.8 mL/1 mL
INACTIVE INGREDIENTS: GLYCERIN 0.0145 mL/1 mL; HYDROGEN PEROXIDE 0.00125 mL/1 mL; WATER 0.18425 mL/1 mL

ADVANCED HAND SANITIZER

Drug facts

Active Ingredient (s)

Ethyl alcohol 80% v/v

Purpose

Antiseptic

Use(s)

Hand Sanitizer to help reduce bacteria on the skin when water and soap are not available.

WARNINGS

For external use only. Flammable. Keep away from heat or flame

Do not use

- Children under 6 years of a age should be supervise when using this product
- On open skin wounds

When using this product keep out of eyes, ears and mouth. In case of contact with eyes, rinse eyes thoroughly with water.

Stop use and ask a doctor if irritation or rash occurs for more than 72 hours, consult a doctor.

Keep out of reach of Children. If swallowed, get medical help or contact a Poison control center right away.

Directions

- Place enough product on hands to cover all surfaces. Rub hands together until dry.
- Supervise children under 6 years of age when using this product to avoid swallowing or misuse.

OTHER INFORMATION

- Store between 15-30C (59-86F)
- Avoid freezing and excessive heat above 40C (104F)

Inactive Ingredients

glycerin, hydrogen, peroxide, purified water USP

PRINCIPAL DISPLAY PANEL - 3785 ML Bottle Label

BIOMINERALES
PHARMA

ADVANCED
HAND SANITIZER

Kills more than 99.99% of germs

Prevention:
Keep away from heat/sparks/open flames/hot surfaces. - No smoking.
Keep container tightly closed.

Response:
IF IN EYES: Rinse cautiously with water for several minutes. Remove
contact lenses, if present and easy to do. Continue rinsing. If eye
irritation persists: Get medical advice/ attention. In case of fire: Use
dry sand, dry chemical or alcohol-resistant foam for extinction.

Storage:
Store in a well-ventilated place. Keep cool.

Disposal:
Dispose of contents/ container to an approved waste disposal plant.

Active ingredients
Ethyl Alcohol 80%
Glycerin 1.45%
Hydrogen Peroxide .125%
Sterilized water 18.425%

Net Contents 3785 ML

Made in the USA